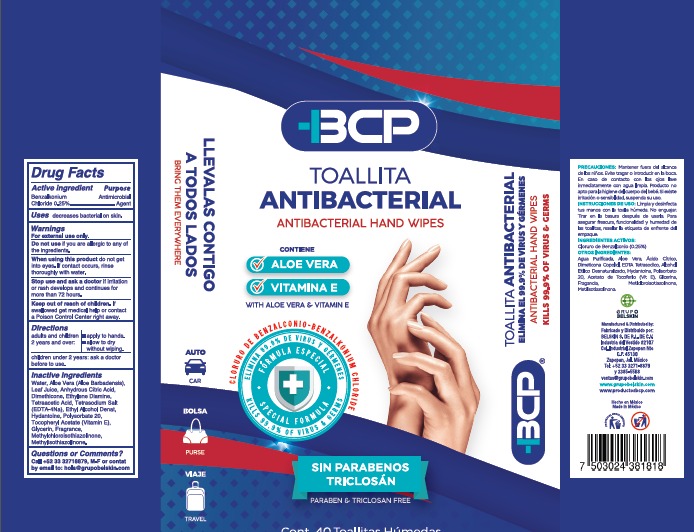 DRUG LABEL: MEDICALLY MINDED
NDC: 78502-6000 | Form: CLOTH
Manufacturer: BELSKIN S. DE, R.L. DE C.V
Category: otc | Type: HUMAN OTC DRUG LABEL
Date: 20200704

ACTIVE INGREDIENTS: BENZALKONIUM CHLORIDE 0.25 g/100 g; ALCOHOL 5 g/100 g
INACTIVE INGREDIENTS: WATER 93.885 g/100 g; ALOE VERA LEAF 0.05 g/100 g; GLYCERIN 0.5 g/100 g; METHYLISOTHIAZOLINONE 0.1 g/100 g; DIMETHICONE 0.005 g/100 g; EDETATE SODIUM TETRAHYDRATE 0.008 g/100 g; METHYLCHLOROISOTHIAZOLINONE 0.1 g/100 g; HYDANTOIN 0.002 g/100 g; ANHYDROUS CITRIC ACID 0.015 g/100 g; POLYSORBATE 20 0.005 g/100 g; .ALPHA.-TOCOPHEROL ACETATE, D- 0.08 g/100 g

ANTICEPTIC WET WIPES

DOSAGE AND ADMINISTRATION

APPLY TO HANDS

ALLOW TO DRY WITHOUT WIPING

WARNINGS AND PRECAUTIONS

WHEN USING THIS PRODUCT DO NOT GET INTO EYES. IF CONTACT OCCURS, RINSE THOROUGHLY WITH WATER.

CHILDREN UNDER 2 YEARS ASK A DOCTOR BEFORE USE

WARNINGS

FOR EXTERNAL USE ONLY

KEEP OUT OF REACH OF CHILDREN. IF SWALLOWED GET MEDICAL HELP OR CONTACT A POISON CONTROL CENTER RIGHT AWAY.

STOP USE AND ASK A DOCTOR IF IRRITATION OR RASH DEVELOPS AND CONTINUES FOR MORE THAN 72 HOURS.

PURPOSE

ANTIMICROBIAL AGENT

ACTIVE INGREDIENT

BENZALKONIUM CHLORIDE

ETHYL ALCOHOL

INACTIVE INGREDIENT

WATER
ALOE VERA (ALOE BARBADENSIS) LEAF JUICE
ANHYDROUS CITRIC ACID
DIMETHICONE
ETHYLENE DIAMINE TETRAACETIC ACID TETRASODIUM SALT (EDTA-4Na)
HYDANTOINE
POLYSORBATE 20
TOCOPHERYL ACETATE (VITAMIN E)
GLYCERIN
FRAGRANCE
METHYLCHLOROISOTHIAZOLINONE
METHYLISOTHIAZOLINONE

INDICATIONS AND USAGE

APPLY TO HANDS

ALLOW TO DRY WITHOUT WIPING